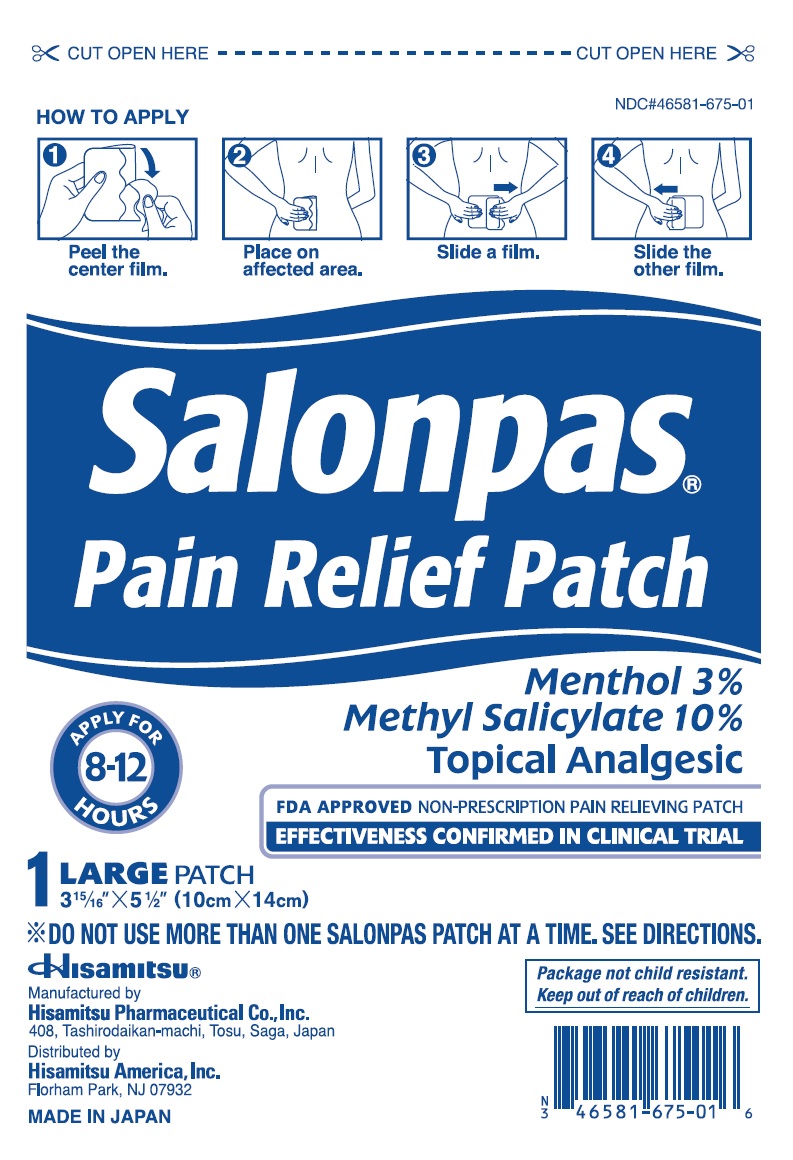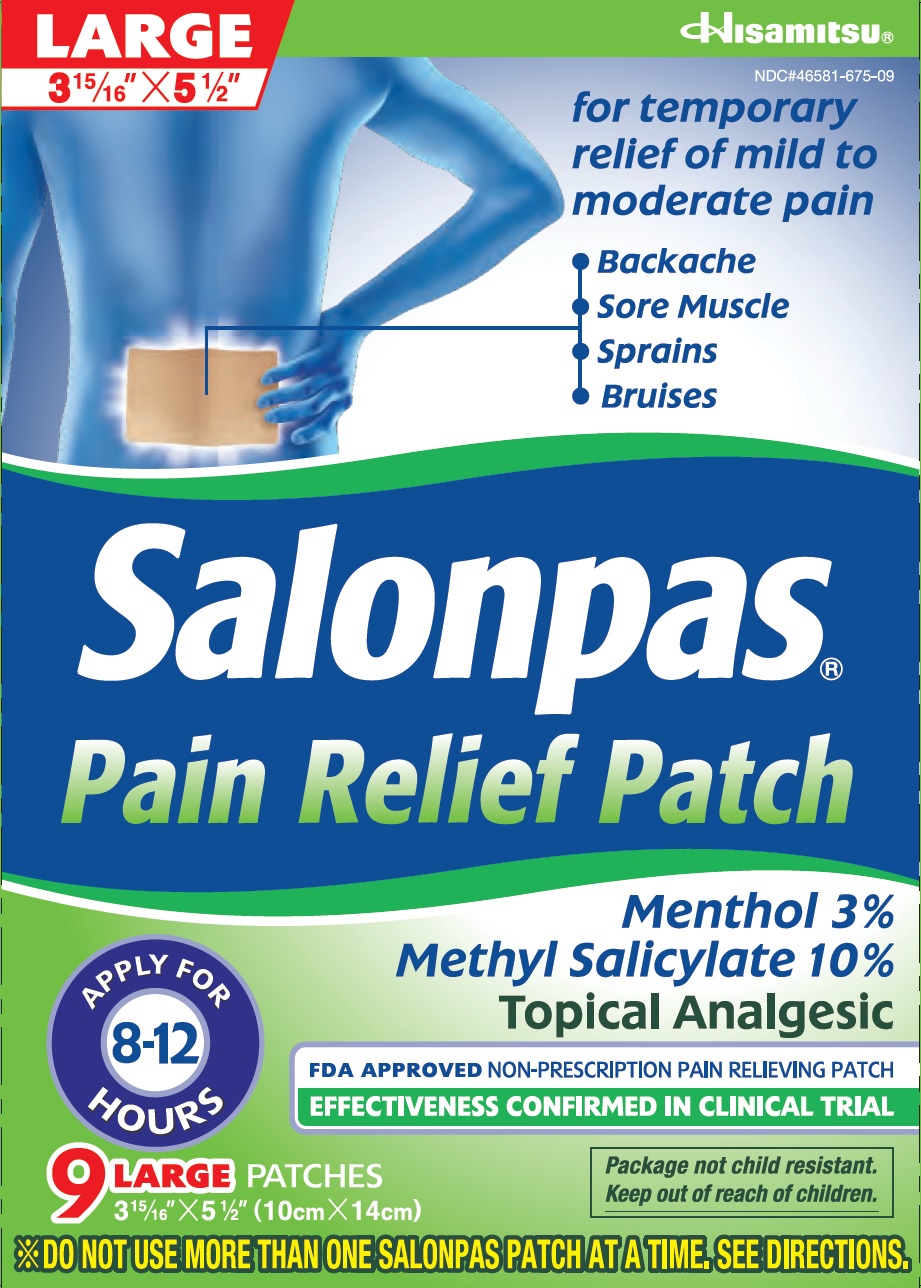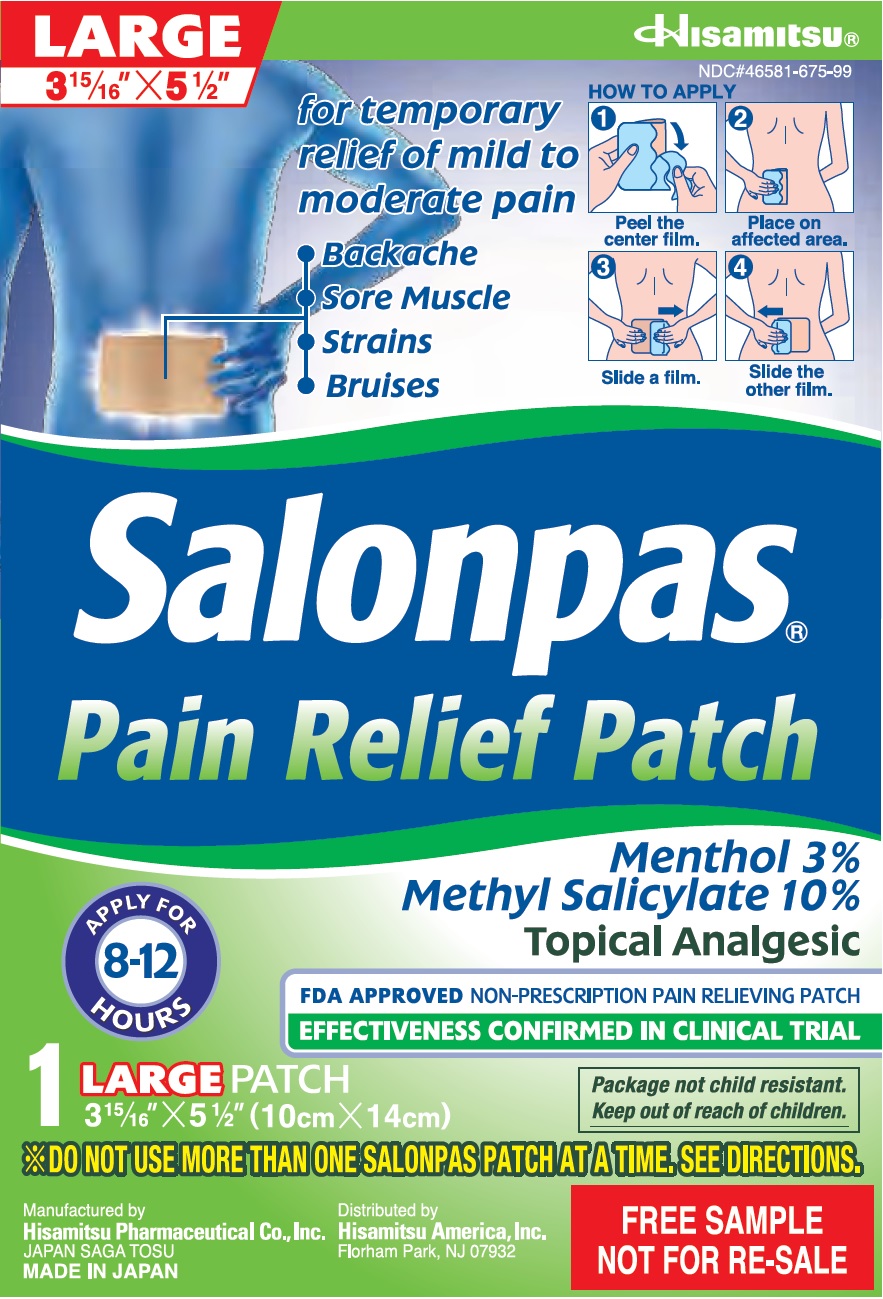 DRUG LABEL: Salonpas Pain Relief
NDC: 46581-675 | Form: PATCH
Manufacturer: Hisamitsu Pharmaceutical Co., Inc.
Category: otc | Type: HUMAN OTC DRUG LABEL
Date: 20250314

ACTIVE INGREDIENTS: MENTHOL 63 mg/1 1; METHYL SALICYLATE 210 mg/1 1
INACTIVE INGREDIENTS: ALUMINUM SILICATE; MINERAL OIL

Active ingredients (in each patch)

Menthol 3%
Methyl salicylate 10% (NSAID : nonsteroidal anti-inflammatory drug)

Purpose

Topical analgesic

Uses

Temporarily relieves mild to moderate aches and pains of muscles and joints associated with:

- strains
- sprains
- simple backache
- arthritis
- bruises

Warnings

For external use only

Stomach bleeding warning:

This product contains an NSAID, which may cause stomach bleeding. The chance is small but higher if you:

- are age 60 or older
- have had stomach ulcers or bleeding problems
- take a blood thinning (anticoagulant) or steroid drug
- take other drugs containing an NSAID [aspirin, ibuprofen, naproxen, or others]
- have 3 or more alcoholic drinks every day while using this product
- take more or for a longer time than directed

Do not use

- on the face or rashes
- on wouds or damaged skin
- if allergic to aspirin or other NSAIDs
- with a heating pad
- when sweating (such as from exercise or heat)
- any patch from a pouch that has been open for 14 or more days
- right before or after heart surgery

Ask a doctor before use if

- you are allergic to topical products
- the stomach bleeding warning applies to you
- you are taking a diuretic
- you have high blood pressure, heart disease, or kidney disease

When using this product

- wash hands after applying or removing patch. Avoid contact with eyes. If eye contact occurs, rinse thoroughly with water.
- the risk of heart attack or stroke may increase if you use more than directed or for longer than directed

Stop use and ask a doctor if

- stomach pain or upset gets worse or lasts
- you feel faint, vomit blood, or have bloody or black stools. These are signs of stomach beeding.
- rash, itching or skin irritaion develops
- condition worsens
- symptoms last for more than 3 days
- symptoms clear up and occur again within a few days

If pregnant or breast-feeding,

ask a health professional before use. It is especially important not to use methyl salicylate at 20 weeks or later in pregnancy unless definitely directed to do so by a doctor because it may cause problems in the unborn child or complications during delivery.

Keep out of reach of children.

If put in mouth, get medical help or contact a Poison Control Center right away. Package not child resistant. Dispose of the used patches after folding sticky ends together.

Directions

Adults 18 years and older:

- only use one patch at a time
- clean and dry affected area
- remove patch from backing film and apply to skin (see illustration)
- apply one patch to the affected area and leave in place for up to 8 to 12 hours
- if pain lasts after using the first patch, a second patch may be applied for up to another 8 to 12 hours
- do not use more than 2 patches per day
- do not use for more than 3 days in a row
- the used patch should be removed from the skin when a new one is applied

Children under 18 years of age: do not use; this product has not been shown to work in children

Other information

- store at 20 - 25 degrees Celsius (68-77 degrees Fahrenheit)
- avoid storing product in direct sunlight
- protect product from excessive moisture
- some individuals may not experience pain relief until several hours after applying the patch

Inactive inredients

alicyclic saturated hydrocarbon resin, baking cloth, film, mineral oil, polyisobutylene, polyisobutylene 1,200,000, styrene-isoprene-styrene block copolymer, synthetic aluminum silicate

Questions or comments?

Toll free 1-87-SALONPASwww.salonpas.us

Principal Display Panel

LARGE
3 15/16" X 5 1/2"
Hisamitsu
NDC#46581-675-09
for temporary relief of mild to moderate pain

Backache
Sore Muscle
Sprains
Bruises
Salonpas
Pain Relief Patch
APPLY FOR 8 - 12 HOURS
Menthol 3%
Methyl Salicylate 10%
Topical Analgesic
FDA APPROVED NON-PRESCRIPTION PAIN RELIEVING PATCH
EFFECTIVENESS CONFIRMED IN CLINICAL TRIAL
9 LARGE PATCHES
3 15/16" X 5 1/2" (10cm X 14cm)
Package not child resistant.
Keep out of reach of children.
*DO NOT USE MORE THAN ONE SALONPAS PATCH AT A TIME. SEE DIRECTIONS.

Principal Display Panel

CUT OPEN HERE

NDC#46581-675-01

HOW TO APPLY
1 Peel the center film.
2 Place on affected area.
3 Slide a film.
4 Slide the other film.

Salonpas
Pain Relief Patch

APPLY FOR 8 - 12 HOURS

Menthol 3%
Methyl Salicylate 10%

Topical Analgesic

FDA APPROVED NON-PRESCRIPTION PAIN RELIEVING PATCH
EFFECTIVENESS CONFIRMED IN CLINICAL TRIAL

1 LARGE PATCH
3 15/16" X 5 1/2" (10cm X 14cm)

*DO NOT USE MORE THAN ONE SALONPAS PATCH AT A TIME. SEE DIRECTIONS.

Hisamitsu

Package not child resistant.
Keep out of reach of children.

Manufactured by
Hisamitsu Pharmaceutical Co., Inc.
408, Tashirodaikan-machi, Tosu, Saga, Japan

Distributed by
Hisamitsu America, Inc.
Florham Park, NJ 07932

MADE IN JAPAN

Principal Display Panel

LARGE
3 15/16" X 5 1/2"
Hisamitsu
NDC#46581-675-99
for temporary relief of mild to moderate pain

Backache
Sore Muscle
Strains
Bruises
HOW TO APPLY
1 Peel the center film.
2 Place on affected area.
3 Slide a film.
4 Slide the other film.
Salonpas
Pain Relief Patch
APPLY FOR 8 - 12 HOURS
Menthol 3%
Methyl Salicylate 10%
Topical Analgesic
FDA APPROVED NON-PRESCRIPTION PAIN RELIEVING PATCH
EFFECTIVENESS CONFIRMED IN CLINICAL TRIAL
1 LARGE PATCH
3 15/16" X 5 1/2" (10cm X 14cm)
Package not child resistant.
Keep out of reach of children.
*DO NOT USE MORE THAN ONE SALONPAS PATCH AT A TIME. SEE DIRECTIONS.
Manufactured by
Hisamitsu Pharmaceutical Co., Inc.
JAPAN SAGA TOSU
MADE IN JAPAN
Distributed by
Hisamitsu America, Inc.
Florham Park, NJ 07932
FREE SAMPLE
NOT FOR RE-SALE